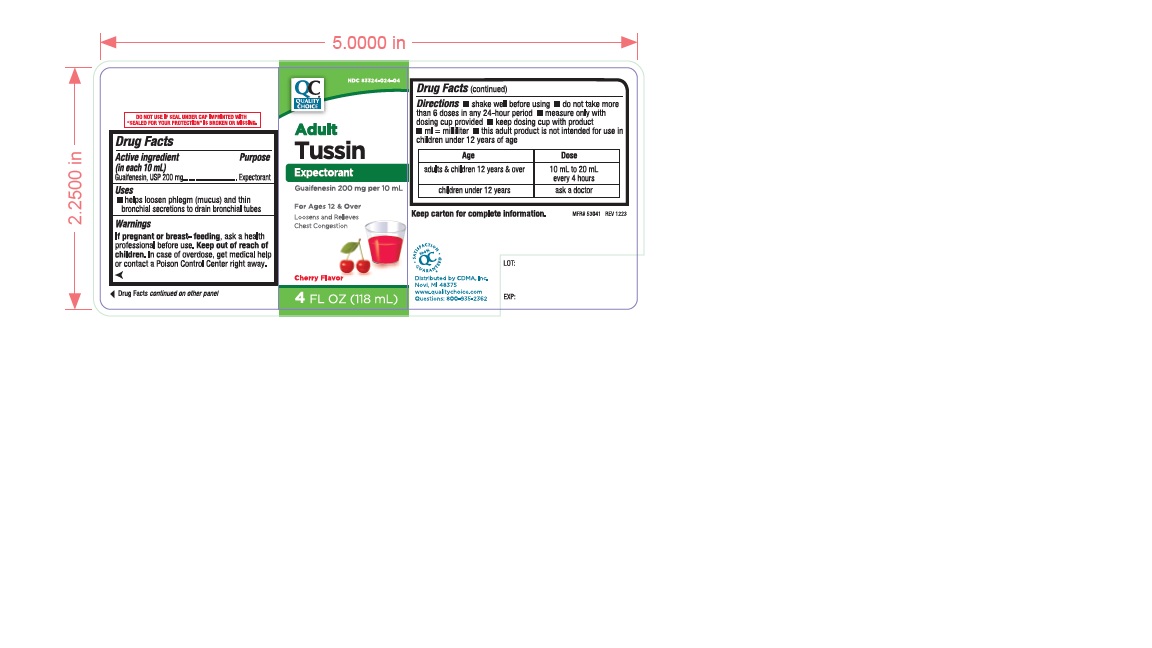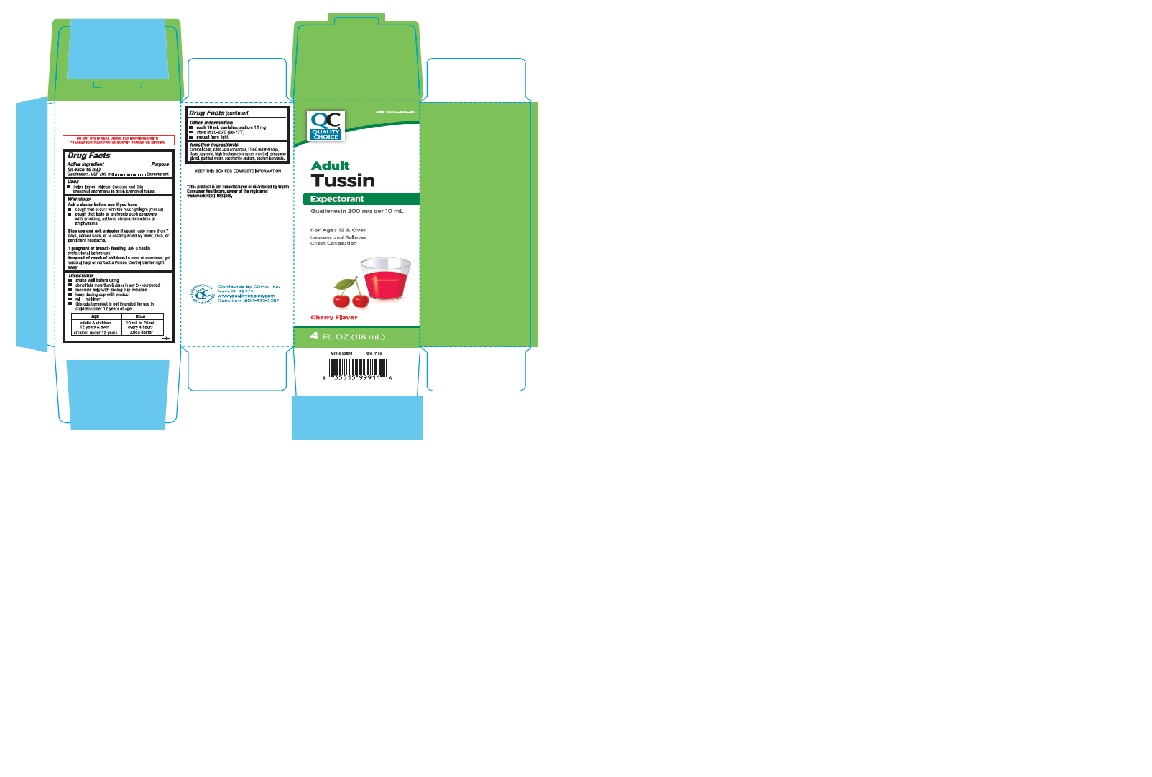 DRUG LABEL: QCH Adult Tussin 541
NDC: 83324-024 | Form: LIQUID
Manufacturer: Chain Drug Marketing Association Inc.
Category: otc | Type: Human OTC Drug Label
Date: 20240502

ACTIVE INGREDIENTS: GUAIFENESIN 200 mg/10 mL
INACTIVE INGREDIENTS: ANHYDROUS CITRIC ACID; FD&C RED NO. 40; GLYCERIN; MENTHOL; HIGH FRUCTOSE CORN SYRUP; PROPYLENE GLYCOL; WATER; SACCHARIN SODIUM; SODIUM BENZOATE; CARAMEL

QCH Adult Tussin 541

ACTIVE INGREDIENT(S)

Guaifenesin, USP 200 mg

PURPOSE

Expectorant

USE(S)

- helps loosen phlegm(mucus) and thin bronchial secretions to drain bronchial tubes

WARNINGS

.

ASK A DOCTOR BEFORE USE IF

- cough that occurs with too much phlegm(mucus)
- cough that lasts or is chronic such as occurs with smoking, asthma, chronic bronchitis or emphysema

STOP USE AND ASK DOCTOR IF

cough lasts more than 7 days, comes back, or is accompanied by fever, rash, or persistent headache.

IF PREGNANT OR BREAST-FEEDING,

ask a health professional before use.

KEEP OUT OF REACH OF CHILDREN

In case of overdose, get medical help or contact a Poison Control Center right away.

DIRECTIONS

shake well before using

do not take more than 6 doses in any 24-hour period

measure only with dosing cup provided

keep dosing cup with product

ml=milliliter

this adult product is not intended for use in children under 12 years of age

Age | Dose
adults & children 12 years & over | 10 mL to 20 mL every 4 hours
children under 12 years | ask a doctor

OTHER INFORMATION

- each 10 mL contains: sodium 12 mg
- store at 20-25oC(68-77oF)
- protect from light

INACTIVE INGREDIENTS

caramel color, citric acid anhydrous, FD&C red# 40 dye, flavor, glycerin, high fructose corn syrup, menthol, propylene glycol, purified water, saccharine sodium, sodium benzoate.

PRINCIPAL DISPLAY PANEL

NDC 83324-024-04

QUALITY CHOICE

Adult Tussin

Expectorant

Guaifenesin 200 mg per 10 mL

For Ages 12 & Over

Loosens and Relieves

Chest Congestion

Cherry Flavor

4FL OZ(118 mL)